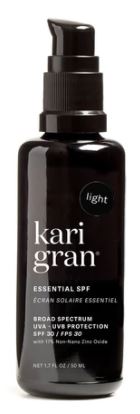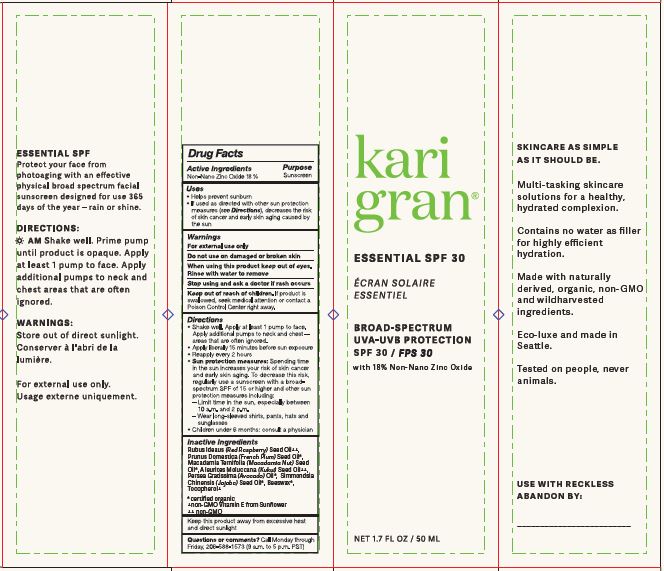 DRUG LABEL: KARI GRAN ESSENTIAL SPF
NDC: 73665-102 | Form: SOLUTION
Manufacturer: KARI GRAN
Category: otc | Type: HUMAN OTC DRUG LABEL
Date: 20251218

ACTIVE INGREDIENTS: ZINC OXIDE 18 g/100 mL
INACTIVE INGREDIENTS: TITANIUM DIOXIDE; MICA; FERROSOFERRIC OXIDE; FERRIC OXIDE YELLOW; ULTRAMARINE BLUE; KUKUI NUT OIL; RASPBERRY SEED OIL; PLUM SEED OIL; MACADAMIA OIL; AVOCADO OIL; JOJOBA OIL; YELLOW WAX; TOCOPHEROL; FERRIC OXIDE RED

KARI GRAN - ESSENTIAL SPF 30, TINTED AND UNTINTED - (73665-102)

ACTIVE INGREDIENT

NON-NANO ZINC OXIDE 18%

PURPOSE

SUNSCREEN

USES

- HELPS PREVENT SUNBURN
- IF USED AS DIRECTED WITH OTHER SUN PROTECTION MEASURES (SEE DIRECTIONS), DECREASES THE RISK OF SKIN CANCER AND EARLY SKIN AGING CAUSED BY THE SUN.

WARNINGS

FOR EXTERNAL USE ONLY.

DO NOT USE ON DAMAGED OR BROKEN SKIN.

WHEN USING THIS PRODUCT KEEP OUT OF EYES. RINSE WITH WATER TO REMOVE.

STOP USE AND ASK A DOCTOR IF RASH OCCURS.

KEEP OUT OF REACH OF CHILDREN. IF PRODUCT IS SWALLOWED, SEEK MEDICAL ATTENTION OR CONTACT A POISON CONTROL CENTER RIGHT AWAY.

DIRECTIONS

- SHAKE WELL. APPLY AT LEAST 1 PUMP TO FACE. APPLY ADDITIONAL PUMPS TO NECK AND CHEST - AREAS THAT ARE OFTEN IGNORED.
- APPLY LIBERALLY 15 MINUTES BEFORE SUN EXPOSURE.
- REAPPLY EVERY 2 HOURS
- SUN PROTECTION MEASURES: SPENDING TIME IN THE SUN INCREASES YOUR RISK OF SKIN CANCER AND EARLY SKIN AGING. TO DECREASE THIS RISK, REGULARLY USE A SUNSCREEN WITH A BROAD-SPECTRUM SPF OF 15 OR HIGHER AND OTHER SUN PROTECTION MEASURES INCLUDING:
- LIMIT TIME IN THE SUN, ESPECIALLY BETWEEN 10 A.M. AND 2 P.M.
- WEAR LONG-SLEEVED SHIRTS, PANTS, HATS AND SUNGLASSES
- CHILDREN UNDER 6 MONTHS: CONSULT A PHYSICIAN

INACTIVE INGREDIENTS

UNTINTED: Rubus Ideaus (Red Raspberry) Seed Oil++, Prunus Domestica (French Plum) Seed Oil*, Macadamia Ternifolia (Macadamia Nut) Seed Oil*, Aleurites Moluccana (Kukui) Seed Oil++, Persea Gratissima (Avocado) Oil*, Simmondsia Chinensis (Jojoba) Seed Oil*, Beeswax*, Tocopherol+

TINTED, LIGHT: Rubus Ideaus (Red Raspberry) Seed Oil++, Prunus Domestica (French Plum) Seed Oil*, Macadamia Ternifolia (Macadamia Nut) Seed Oil*, Aleurites Moluccana (Kukui) Seed Oil++, Persea Gratissima (Avocado) Oil*, Simmondsia Chinensis (Jojoba) Seed Oil*, Beeswax*, Tocopherol+, Titanium Dioxide, Iron Oxides, Mica.

TINTED, MEDIUM: Rubus Ideaus (Red Raspberry) Seed Oil++, Prunus Domestica (French Plum) Seed Oil*, Macadamia Ternifolia (Macadamia Nut) Seed Oil*, Aleurites Moluccana (Kukui) Seed Oil++, Persea Gratissima (Avocado) Oil*, Simmondsia Chinensis (Jojoba) Seed Oil*, Beeswax*, Tocopherol+, Titanium Dioxide, Iron Oxides, Mica.

TINTED, DARK: Rubus Ideaus (Red Raspberry) Seed Oil++, Prunus Domestica (French Plum) Seed Oil*, Macadamia Ternifolia (Macadamia Nut) Seed Oil*, Aleurites Moluccana (Kukui) Seed Oil++, Persea Gratissima (Avocado) Oil*, Simmondsia Chinensis (Jojoba) Seed Oil*, Beeswax*, Tocopherol+, Titanium Dioxide, Iron Oxides, Mica, Ultramarines.

*certiﬁed organic
+non-GMO Vitamin E from Sunﬂower
++ non-GMO

STORAGE AND HANDLING

KEEP THIS PRODUCT AWAY FROM EXCESSIVE HEAT AND DIRECT SUNLIGHT

QUESTIONS OR COMMENTS?

CALL MONDAY THROUGH FRIDAY, 206-588-1573 (9 A.M. TO 5 P.M. PST)